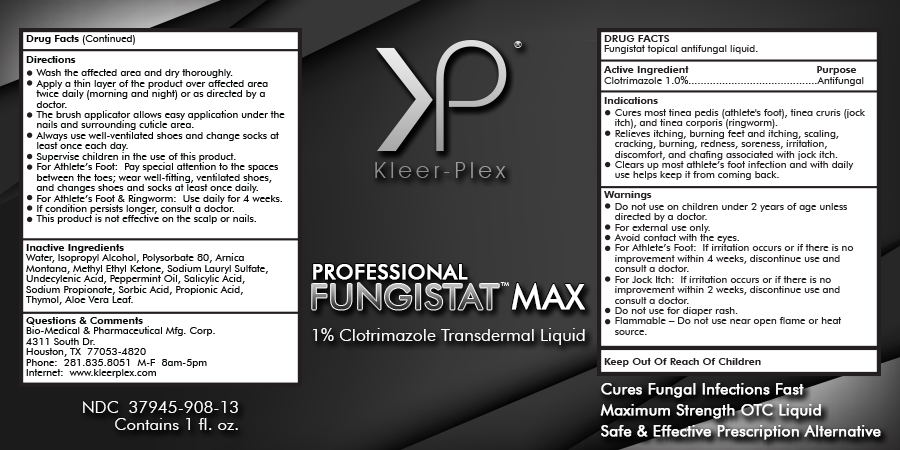 DRUG LABEL: Fungistat Max
NDC: 37945-908 | Form: LIQUID
Manufacturer: Bio-Medical & Pharmaceutical Manufacturing Corporation
Category: otc | Type: HUMAN OTC DRUG LABEL
Date: 20160405

ACTIVE INGREDIENTS: CLOTRIMAZOLE 10 mg/1 mL
INACTIVE INGREDIENTS: WATER; POLYSORBATE 80; ARNICA MONTANA; UNDECYLENIC ACID; PEPPERMINT OIL; SALICYLIC ACID; SODIUM PROPIONATE; SODIUM LAURYL SULFATE; SORBIC ACID; PROPIONIC ACID; THYMOL; ALOE VERA LEAF; ISOPROPYL ALCOHOL; METHYL ETHYL KETONE

Drug Facts

Fungistat topical antifungal liquid.

Active Ingredient

Clotrimazole 1.0%

Purpose

Antifungal

Indications

- Cures most tinea pedis (athlete's foot), tinea cruris (jock itch), and tinea corporis (ringworm).
- Relieves itching, burning feet and itching, scaling, cracking, burning, redness, soreness, irritation, discomfort, and chafing associated with jock itch.
- Clears up most athlete’s foot infection and with daily use helps keep it from coming back.

Warnings

- Do not use on children under 2 years of age unless directed by a doctor.
- For external use only.
- Avoid contact with the eyes.
- For Athlete’s Foot: If irritation occurs or if there is no improvement within 4 weeks, discontinue use and consult a doctor.
- For Jock Itch: If irritation occurs or if there is no improvement within 2 weeks, discontinue use and consult a doctor.
- Do not use for diaper rash.
- Flammable – Do not use near open flame or heat source.

Directions

- Wash the affected area and dry thoroughly.
- Apply a thin layer of the product over affected area twice daily (morning and night) or as directed by a doctor.
- The brush applicator allows easy application under the nails and surrounding cuticle area.
- Always use well-ventilated shoes and change socks at least once each day.
- Supervise children in the use of this product.
- For Athlete’s Foot: Pay special attention to the spaces between the toes; wear well-fitting, ventilated shoes, and changes shoes and socks at least once daily.
- For Athlete’s Foot & Ringworm: Use daily for 4 weeks.
- If condition persists longer, consult a doctor.
- This product is not effective on the scalp or nails.

Inactive Ingredients

Water, Isopropyl Alcohol, Polysorbate 80, Arnica Montana, Methyl Ethyl Ketone, Sodium Lauryl Sulfate, Undecylenic Acid, Peppermint Oil, Salicylic Acid, Sodium Propionate, Sorbic Acid, Propionic Acid, Thymol, Aloe Vera Leaf.

Questions or Comments

Bio-Medical & Pharmaceutical Mfg. Corp.

4311 South Dr.

Houston, TX 77053-4820

Phone: 281.835.8051 M-F 8am-5pm

Internet: www.kleerplex.com

PACKAGE LABEL

Kleer-Plex

PROFESSIONAL FUNGISTAT MAX

1% Clotrimazole Transdermal Liquid

NDC 37945-908-13

Contains 1 fl. oz.

Cures Fungal Infections Fast

Maximum Strenth OTC Liquid

Safe & Effective Prescription Alternative